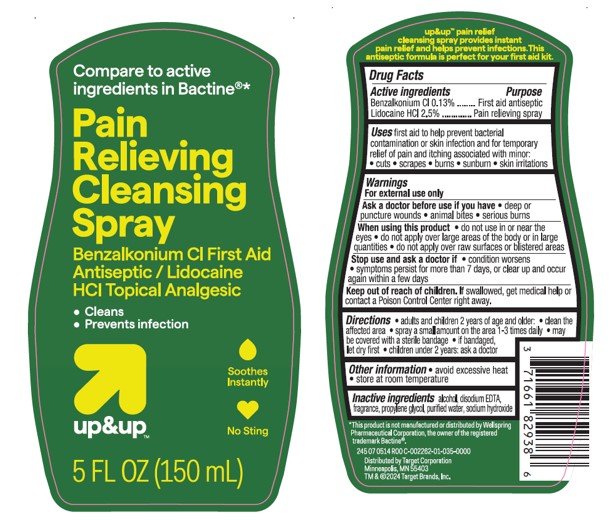 DRUG LABEL: Target Up and Up Pain Relieving Cleansing
NDC: 11673-252 | Form: SPRAY
Manufacturer: TARGET CORPORATION
Category: otc | Type: HUMAN OTC DRUG LABEL
Date: 20240125

ACTIVE INGREDIENTS: BENZALKONIUM CHLORIDE 0.13 g/100 mL; LIDOCAINE HYDROCHLORIDE 2.5 g/100 mL
INACTIVE INGREDIENTS: WATER; SODIUM HYDROXIDE; EDETATE DISODIUM; ALCOHOL; PROPYLENE GLYCOL

Target Up and Up Pain Relieving Cleansing Spray

Active Ingredients

Benzalkonium Cl 0.13%

Lidocaine HCL 2.5%

Purpose

First aid antiseptic

Pain relieving spray

Uses

first aid to help prevent bacterial contamination or skin infection and for temporary relief of pain and itching associated with minor:

- cuts
- scrapes
- minor burns
- sunburn
- minor skin irritations

Warnings

For external use only

Ask a doctor before use if you have

- deep or puncture wounds
- animal bites
- serious burns

When using this product

- do not use in or near the eyes
- do not apply over large areas of the body or in large quantities
- do not apply over raw surfaces or blistered areas

Stop use and ask a doctor if

- condition worsens
- symptoms persist for more than 7 days, or clear up and occur again within a few days

Keep out of reach of children.

If swallowed, get medical help or contact a Poison Control Center right away.

Directions

- adults and children 2 years and older:
- clean the affected area; apply a small amount on the area 1-3 times daily
- may be covered with a sterile bandage
- if bandaged, llet dry first
- children under 2 years, ask a doctor

Other information

- avoid excessive heat
- store at room temperature

Inactive ingredients

alcohol, disodium EDTA, fragrance, propylene glycol, purified water, sodium hydroxide